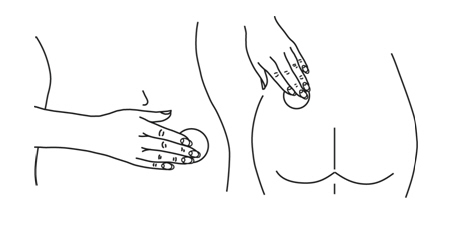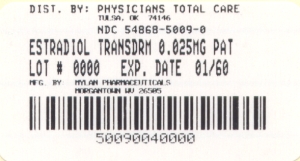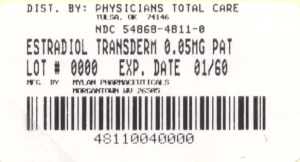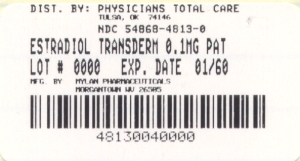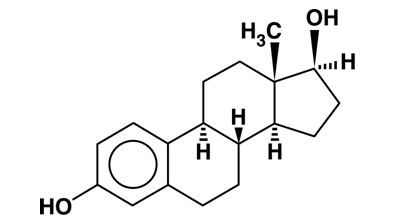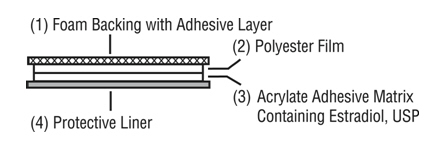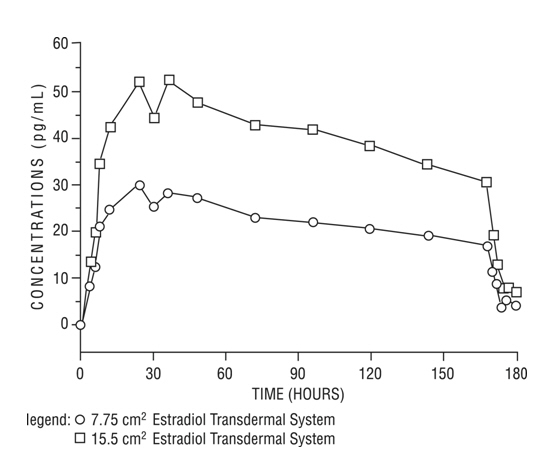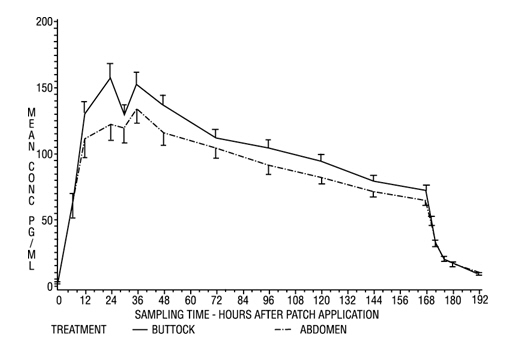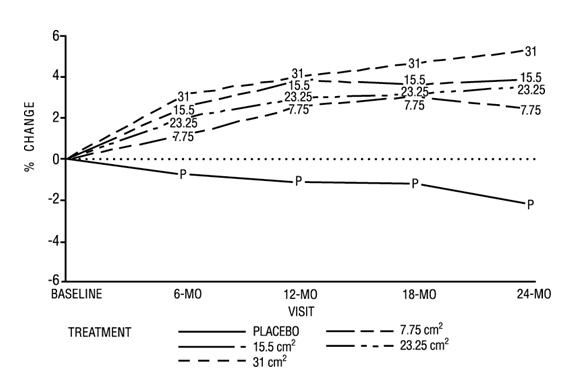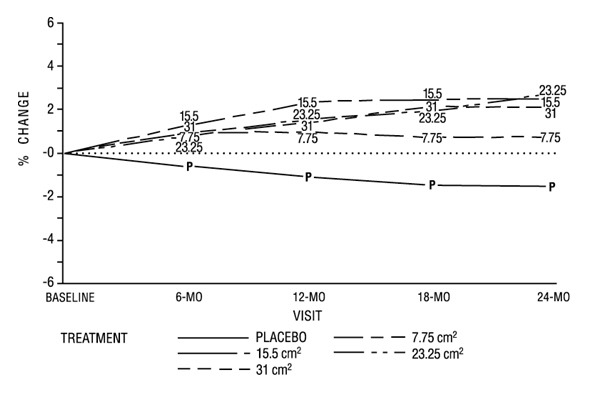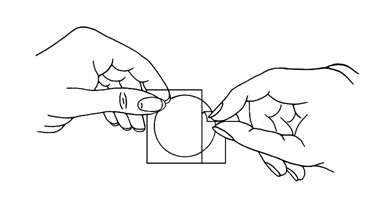 DRUG LABEL: Estradiol
NDC: 54868-4811 | Form: PATCH
Manufacturer: Physicians Total Care, Inc.
Category: prescription | Type: HUMAN PRESCRIPTION DRUG LABEL
Date: 20100118

ACTIVE INGREDIENTS: ESTRADIOL 0.97 mg/48 [USP'U]
INACTIVE INGREDIENTS: PROPYLENE GLYCOL; POVIDONE; SILICON DIOXIDE

PRESCRIBING INFORMATION Estradiol Transdermal System Continuous Delivery (Once-Weekly), USP

BOXED WARNING

ESTROGENS INCREASE THE RISK OF ENDOMETRIAL CANCER

Close clinical surveillance of all women taking estrogens is important. Adequate diagnostic measures, including endometrial sampling when indicated, should be undertaken to rule out malignancy in all cases of undiagnosed persistent or recurring abnormal vaginal bleeding.

There is no evidence that the use of “natural” estrogens results in a different endometrial risk profile than synthetic estrogens of equivalent estrogen doses. (See WARNINGS, Malignant neoplasms, Endometrial cancer.)

CARDIOVASCULAR AND OTHER RISKS

Estrogens with and without progestins should not be used for the prevention of cardiovascular disease or dementia. (See WARNINGS, Cardiovascular disorders and Dementia.)

The Women’s Health Initiative (WHI) study reported increased risks of myocardial infarction, stroke, invasive breast cancer, pulmonary emboli, and deep vein thrombosis in postmenopausal women (50 to 79 years of age) during 5 years of treatment with oral conjugated estrogens (CE 0.625 mg) combined with medroxyprogesterone acetate (MPA 2.5 mg) relative to placebo. (See CLINICAL PHARMACOLOGY, Clinical Studies and WARNINGS, Cardiovascular disorders and Malignant neoplasms, Breast cancer.)

The Women’s Health Initiative Memory Study (WHIMS), a substudy of WHI, reported increased risk of developing probable dementia in postmenopausal women 65 years of age or older during 4 years of treatment with oral conjugated estrogens plus medroxyprogesterone acetate relative to placebo. It is unknown whether this finding applies to younger postmenopausal women. (See CLINICAL PHARMACOLOGY, Clinical Studies and WARNINGS, Dementia and PRECAUTIONS, Geriatric Use.)

Other doses of oral conjugated estrogens with medroxyprogesterone acetate, and other combinations and dosage forms of estrogens and progestins were not studied in the WHI clinical trials and, in the absence of comparable data, these risks should be assumed to be similar. Because of these risks, estrogens with or without progestins should be prescribed at the lowest effective doses and for the shortest duration consistent with treatment goals and risks for the individual woman.

DESCRIPTION

Estradiol Transdermal System Continuous Delivery (Once-Weekly) is designed to release estradiol continuously upon application to intact skin. Six (7.75 cm^2, 11.625 cm^2, 15.5 cm^2, 18.6 cm^2, 23.25 cm^2 and 31 cm^2) systems are available to provide nominal in vivo delivery of 0.025 mg, 0.0375 mg, 0.05 mg, 0.06 mg, 0.075 mg or 0.1 mg respectively of estradiol per day. The period of use is 7 days. Each system has a contact surface area of either 7.75 cm^2, 11.625 cm^2, 15.5 cm^2, 18.6 cm^2, 23.25 cm^2 or 31 cm^2, and contains 0.97 mg, 1.46 mg, 1.94 mg, 2.33 mg, 2.91 mg or 3.88 mg of estradiol USP respectively. The composition of the systems per unit area is identical. Estradiol USP is a white, crystalline powder, chemically described as estra-1,3,5(10)-triene-3,17ß-diol. It has a molecular formula of C18H2402 and molecular weight of 272.39. The structural formula is:

The Estradiol Transdermal System Continuous Delivery (Once-Weekly) comprises four layers. Proceeding from the visible surface toward the surface attached to the skin, these layers are (1) a foam backing with adhesive layer, (2) a polyester film, and (3) an acrylate adhesive matrix containing estradiol USP. A protective liner (4) of siliconized polyester film is attached to the adhesive surface and must be removed before the system can be used.

The active component of the system is estradiol. The remaining components of the system (propylene glycol, povidone, anhydrous colloidal silicon dioxide, pressure sensitive acrylic adhesive, copolymer foam, polyester film, and brown ink) are pharmacologically inactive.

CLINICAL PHARMACOLOGY

Endogenous estrogens are largely responsible for the development and maintenance of the female reproductive system and secondary sexual characteristics. Although circulating estrogens exist in a dynamic equilibrium of metabolic interconversions, estradiol is the principal intracellular human estrogen and is substantially more potent than its metabolites, estrone and estriol at the receptor level.

The primary source of estrogen in normally cycling adult women is the ovarian follicle, which secretes 70 mcg to 500 mcg of estradiol daily, depending on the phase of the menstrual cycle. After menopause, most endogenous estrogen is produced by conversion of androstenedione, secreted by the adrenal cortex, to estrone by peripheral tissues. Thus, estrone and the sulfate conjugated form, estrone sulfate, are the most abundant circulating estrogens in postmenopausal women.

Estrogens act through binding to nuclear receptors in estrogen-responsive tissues. To date, two estrogen receptors have been identified. These vary in proportion from tissue to tissue.

Circulating estrogens modulate the pituitary secretion of the gonadotropins luteinizing hormone (LH) and follicle-stimulating hormone (FSH), through a negative feedback mechanism. Estrogens act to reduce the elevated levels of these hormones seen in postmenopausal women.

Pharmacokinetics

Transdermal administration of Estradiol Transdermal System Continuous Delivery (Once-Weekly) produces mean serum concentrations of estradiol comparable to those produced by premenopausal women in the early follicular phase of the ovulatory cycle. The pharmacokinetics of estradiol following application of the Estradiol Transdermal System Continuous Delivery (Once-Weekly) were investigated in 197 healthy postmenopausal women in six studies. In five of the studies Estradiol Transdermal System Continuous Delivery (Once-Weekly) was applied to the abdomen and in a sixth study application to the buttocks and abdomen were compared.

Absorption

The Estradiol Transdermal System Continuous Delivery (Once-Weekly) continuously releases estradiol which is transported across intact skin leading to sustained circulating levels of estradiol during a 7 day treatment period. The systemic availability of estradiol after transdermal administration is about 20 times higher than that after oral administration. This difference is due to the absence of first-pass metabolism when estradiol is given by the transdermal route.

In a bioavailability study, the Estradiol Transdermal System Continuous Delivery (Once-Weekly) 7.75 cm^2 was studied with the Estradiol Transdermal System Continuous Delivery (Once-Weekly) 15.5 cm^2 as reference. The mean estradiol levels in serum from the two sizes are shown in Figure 1.

Figure 1 Mean Serum 17ß-Estradiol Concentrations vs. Time Profile following Application of a 7.75 cm^2 Transdermal Patch and Application of a 15.5 cm^2 Estradiol Transdermal System Continuous Delivery (Once-Weekly) Patch

Dose proportionality was demonstrated for the Estradiol Transdermal System Continuous Delivery (Once-Weekly) 7.75 cm^2 transdermal system as compared to the Estradiol Transdermal System Continuous Delivery (Once-Weekly) 15.5 cm^2 transdermal system in a 2 week crossover study with a 1 week washout period between the two transdermal systems in 24 postmenopausal women.

Dose proportionality was also demonstrated for the Estradiol Transdermal System Continuous Delivery (Once-Weekly) (15.5 cm^2 and 31 cm^2) in a 1 week study conducted in 54 postmenopausal women. The mean steady-state levels (Cavg) of the estradiol during the application of Estradiol Transdermal System Continuous Delivery (Once-Weekly) 31 cm^2 and 15.5 cm^2 on the abdomen were about 80 pg/mL and 40 pg/mL, respectively.

In a 3 week multiple application study in 24 postmenopausal women, the 31 cm^2 Estradiol Transdermal System Continuous Delivery (Once-Weekly) produced average peak estradiol concentrations (Cmax) of approximately 100 pg/mL. Trough values at the end of each wear interval (Cmin) were approximately 35 pg/mL. Nearly identical serum curves were seen each week, indicating little or no accumulation of estradiol in the body. Serum estrone peak and trough levels were 60 pg/mL and 40 pg/mL, respectively.

In a single-dose, randomized, crossover study conducted to compare the effect of site of application, 38 postmenopausal women wore a single Estradiol Transdermal System Continuous Delivery (Once-Weekly) 31 cm^2 system for one week on the abdomen and buttocks. The estradiol serum concentration profiles are shown in Figure 2. Cmax and Cavg values were, respectively, 25% and 17% higher with the buttock application than with the abdomen application.

Figure 2 Observed Mean (± S.E.) Estradiol Serum Concentrations for a One Week Application of the Estradiol Transdermal System Continuous Delivery (Once-Weekly) (31 cm^2) to the abdomen and buttocks of 38 postmenopausal women

Table 1 provides a summary of estradiol pharmacokinetic parameters determined during evaluation of Estradiol Transdermal System Continuous Delivery (Once-Weekly).

Table 1 Pharmacokinetic Summary (Mean Estradiol Values)
Estradiol Delivery Rate | Surface Area (cm^2) | Application Site | No. of Subjects | Dosing | Cmax (pg/mL) | Cmin (pg/mL) | Cavg (pg/mL)
0.025 | 7.75 | Abdomen | 24 | Single | 32 | 17 | 22
0.05 | 15.5 | Abdomen | 102 | Single | 71 | 29 | 41
0.1 | 31 | Abdomen | 139 | Single | 147 | 60 | 87
0.1 | 31 | Buttock | 38 | Single | 174 | 71 | 106

The relative standard deviation of each pharmacokinetic parameter after application to the abdomen averaged 50%, which is indicative of the considerable intersubject variability associated with transdermal drug delivery. The relative standard deviation of each pharmacokinetic parameter after application to the buttock was lower than that after application to the abdomen (e.g., for Cmax 39% vs. 62%, and for Cavg 35% vs. 48%).

Distribution

The distribution of exogenous estrogens is similar to that of endogenous estrogens.

Estrogens are widely distributed in the body and are generally found in higher concentrations in the sex hormone target organs. Estrogens circulate in the blood largely bound to sex hormone binding globulin (SHBG) and albumin.

Metabolism

Exogenous estrogens are metabolized in the same manner as endogenous estrogens. Circulating estrogens exist in a dynamic equilibrium of metabolic interconversions. These transformations take place mainly in the liver. Estradiol is converted reversibly to estrone, and both can be converted to estriol, which is the major urinary metabolite. Estrogens also undergo enterohepatic recirculation via sulfate and glucuronide conjugation in the liver, biliary secretion of conjugates into the intestine, and hydrolysis in the gut followed by reabsorption. In postmenopausal women, a significant proportion of the circulating estrogens exist as sulfate conjugates, especially estrone sulfate, which serves as a circulating reservoir for the formation of more active estrogens.

Excretion

Estradiol, estrone and estriol are excreted in the urine along with glucuronide and sulfate conjugates.

Special Populations Geriatric

There have not been sufficient numbers of geriatric patients involved in clinical studies utilizing Estradiol Transdermal System Continuous Delivery (Once-Weekly) to determine whether those over 65 years of age differ from younger subjects in their response to Estradiol Transdermal System Continuous Delivery (Once-Weekly).

Pediatric

No pharmacokinetic study for Estradiol Transdermal System Continuous Delivery (Once-Weekly) has been conducted in a pediatric population.

Gender

Estradiol Transdermal System Continuous Delivery (Once-Weekly) is indicated for use in women only.

Race

No studies were done to determine the effect of race on the pharmacokinetics of Estradiol Transdermal System Continuous Delivery (Once-Weekly).

Patients with Renal Impairment

Total estradiol serum levels are higher in postmenopausal women with end stage renal disease (ESRD) receiving maintenance hemodialysis than in normal subjects at baseline and following oral doses of estradiol. Therefore, conventional transdermal estradiol doses used in individuals with normal renal function may be excessive for postmenopausal women with ESRD receiving maintenance hemodialysis.

Patients with Hepatic Impairment

Estrogens may be poorly metabolized in patients with impaired liver function and should be administered with caution.

Drug Interactions

In vitro and in vivo studies have shown that estrogens are metabolized partially by cytochrome P450 3A4 (CYP3A4). Therefore, inducers or inhibitors of CYP3A4 may affect estrogen drug metabolism. Inducers of CYP3A4 such as St. John’s Wort preparations (Hypericum perforatum), phenobarbital, carbamazepine, and rifampin may reduce plasma concentrations of estrogens, possibly resulting in a decrease in therapeutic effects and/or changes in the uterine bleeding profile. Inhibitors of CYP3A4 such as erythromycin, clarithromycin, ketoconazole, itraconazole, ritonavir and grapefruit juice may increase plasma concentrations of estrogens and may result in side effects.

Adhesion

An open-label study of adhesion potentials of placebo transdermal systems that correspond to the 7.75 cm^2 and 15.5 cm^2 sizes of Estradiol Transdermal System Continuous Delivery (Once-Weekly) was conducted in 112 healthy women of 45 to 75 years of age. Each woman applied both transdermal systems weekly, on the upper outer abdomen, for 3 consecutive weeks. It should be noted that lower abdomen and upper quadrant of the buttock are the approved sites of application for Estradiol Transdermal System Continuous Delivery (Once-Weekly).

The adhesion assessment was done visually on Days 2, 4, 5, 6, 7 of each week of transdermal system wear. A total of 1,654 adhesion observations were conducted for 333 transdermal systems of each size.

Of these observations, approximately 90% showed essentially no lift for both the 7.75 cm^2 and 15.5 cm^2 transdermal systems. Of the total number of transdermal systems applied, approximately 5% showed complete detachment for each size. Adhesion potentials of the 23.25 cm^2 and 31 cm^2 sizes of transdermal systems (0.075 mg/day and 0.1 mg/day) have not been studied.

Clinical Studies Effects on vasomotor symptoms

A study of 214 women 25 to 74 years old met the qualification criteria and were randomly assigned to one of the three treatment groups: 72 to the 0.05 mg estradiol patch, 70 to the 0.1 mg estradiol patch, and 72 to placebo. Potential subjects were postmenopausal women in good general health who experienced vasomotor symptoms. Natural menopause patients had not menstruated for at least 12 months and surgical menopause patients had undergone bilateral oophorectomy at least 4 weeks before evaluation for study entry. In order to enter the 11 week treatment phase of the study, potential subjects must have experienced a minimum of five moderate to severe hot flushes per week, or a minimum of 15 hot flushes of any severity per week, for 2 consecutive weeks. Women wore the patches in a cyclical fashion (three weeks on and one week off).

During treatment, all subjects used diaries to record the number and severity of hot flushes. Subjects were monitored by clinic visits at the end of weeks 1, 3, 7, and 11 and by telephone at the end of weeks 4, 5, 8, and 9.

Adequate data for the analysis of efficacy was available from 191 subjects. The results are presented as the mean ± SD number of flushes in each of the 3 treatment weeks of each 4 week cycle. In the 0.05 mg estradiol group, the mean weekly hot flush rate across all treatment cycles decreased from 46 ± 6.5 at baseline to 20 ± 3.0 (-67.0%). The 0.1 mg estradiol group had a decline in the mean weekly hot flush rate from 52 ± 4.4 at baseline to 16 ± 2.4 (-72.0%). In the placebo group, the mean weekly hot flush rate declined from 53 ± 4.5 at baseline to 46 ± 6.5 (-18.1%). Compared with placebo, the 0.05 mg and 0.1 mg estradiol groups showed a statistically significantly larger mean decrease in hot flushes across all treatment cycles (P less than 0.05). When the response to treatment was analyzed for each of the three cycles of therapy, similar statistically significant differences were observed between both estradiol treatment groups and the placebo group during all treatment cycles.

In a double-blind, placebo-controlled, randomized study of 187 women receiving Estradiol Transdermal System Continuous Delivery (Once-Weekly) 0.025 mg/day or placebo continuously for up to three 28 day cycles, the Estradiol Transdermal System Continuous Delivery (Once-Weekly) 0.025 mg/day dosage was shown to be statistically better than placebo at weeks 4 and 12 for relief of both the frequency and severity of moderate to severe vasomotor symptoms.

Table 2 Mean Change from Baseline in the Number of Moderate to Severe Vasomotor Symptoms (ITT)
Treatment Group | Statistics | Week 4 | Week 8 | Week 12
E2 TDS | N | 82 | 84 | 68
 | Mean | -6.45 | -7.69 | -7.56
 | SD | 4.65 | 4.76 | 4.64
Placebo | N | 83 | 71 | 65
 | Mean | -5.11 | -5.98 | -5.98
 | SD | 7.43 | 8.63 | 9.69
 | p-Value | Less than 0.002 |  | Less than 0.003

A second active-control trial of 193 randomized subjects was supportive of the placebo-controlled trial.

Effects on bone mineral density

A two year clinical trial enrolled a total of 175 healthy, hysterectomized, postmenopausal, non-osteoporotic (i.e., lumbar spine bone mineral density less than 0.9 gm/cm^2) women at 10 study centers in the United States. One hundred twenty nine subjects were allocated to receive active treatment with four different doses of estradiol patches (7.75 cm^2, 15.5 cm^2, 23.25 cm^2, 31 cm^2) and 46 subjects were allocated to receive placebo patches. Seventy seven percent of the randomized subjects (100 on active drug and 34 on placebo) contributed data to the analysis of percent change of A-P spine bone mineral density (BMD), the primary efficacy variable (see Figure 3). A statistically significant overall treatment effect at each timepoint was noted, implying bone preservation for all active treatment groups at all timepoints, as opposed to bone loss for placebo at all timepoints.

Figure 3 Mean Percent Change from Baseline in Lumbar Spine (A-P View) Bone Mineral Density by Treatment and Time Last Observation Carried Forward

Percent change in BMD of the total hip (see Figure 4), was also statistically significantly different from placebo for all active treatment groups. The results of the measurements of biochemical markers supported the finding of efficacy for all doses of transdermal estradiol. Serum osteocalcin levels decreased, indicative of a decrease in bone formation, at all timepoints for all active treatment doses, statistically significantly different from placebo (which generally rose). Urinary deoxypyridinoline and pyridinoline changes also suggested a decrease in bone turnover for all active treatment groups.

Figure 4 Mean Percent Change from Baseline in Total Hip by Treatment and Time Last Observation Carried Forward

Footnote: This figure is based on 74% of the randomized subjects (95 on active drug and 34 on placebo).

Women's Health Initiative Studies

The Women’s Health Initiative (WHI) enrolled a total of 27,000 predominantly healthy postmenopausal women to assess the risks and benefits of either the use of oral 0.625 mg conjugated estrogens (CE) per day alone or the use of 0.625 mg conjugated estrogens plus 2.5 mg medroxyprogesterone acetate (MPA) per day compared to placebo in the prevention of certain chronic diseases. The primary endpoint was the incidence of coronary heart disease (CHD) (nonfatal myocardial infarction and CHD death), with invasive breast cancer as the primary adverse outcome studied. A “global index” included the earliest occurrence of CHD, invasive breast cancer, stroke, pulmonary embolism (PE), endometrial cancer, colorectal cancer, hip fracture, or death due to other cause. The study did not evaluate the effects of CE or CE/MPA on menopausal symptoms.

The CE/MPA substudy was stopped early because, according to the predefined stopping rule, the increased risk of breast cancer and cardiovascular events exceeded the specified benefits included in the “global index.” Results of the CE/MPA substudy, which included 16,608 women (average age of 63 years, range 50 to 79; 83.9% White, 6.5% Black, 5.5% Hispanic), after an average follow-up of 5.2 years are presented in Table 3 below:

Table 3 RELATIVE AND ABSOLUTE RISK SEEN IN THE CE/MPA SUBSTUDY OF WHI (*)
Event | Relative Risk CE/MPA vs. Placebo at 5.2 Years (95% CI (*,1) | Placebo N=8102 Absolute Risk per | CE/MPA N=8506 10,000 Person-years
CHD events Nonfatal MI CHD death | 1.29 (1.02-1.63) 1.32 (1.02-1.72) 1.18 (0.70-1.97) | 30 23 6 | 37 30 7
Invasive breast cancer (2) | 1.26 (1.00-1.59) | 30 | 38
Stroke | 1.41 (1.07-1.85) | 21 | 29
Pulmonary embolism | 2.13 (1.39-3.25) | 8 | 16
Colorectal cancer | 0.63 (0.43-0.92) | 16 | 10
Endometrial cancer | 0.83 (0.47-1.47) | 6 | 5
Hip fracture | 0.66 (0.45-0.98) | 15 | 10
Death due to cause others than the events above | 0.92 (0.74-1.14) | 40 | 37
Global Index (3) | 1.15 (1.03-1.28) | 151 | 170
Deep vein thrombosis (4) | 2.07 (1.49-2.87) | 13 | 26
Vertebral fractures (4) | 0.66 (0.44-0.98) | 15 | 9
Other osteoporotic fractures (4) | 0.77 (0.69-0.86) | 170 | 131

(*) adapted from JAMA, 2002; 288:321-333
(1) * nominal confidence intervals unadjusted from multiple looks and multiple comparisons
(2) includes metastatic and non-metastatic breast cancer with the exceptioin of in situ breast cancer
(3) a subset of the events was combined in a "global index", defined as the earliest occurrence of CHD events,
invasive breast cancer, stroke, pulmonary embolism, endometrial cancer, colorectal cancer, hip fracture,
or death due to other causes
(4) not included in Global Index

For those outcomes included in the “global index,” absolute excess risks per 10,000 women-years in the group treated with CE/MPA were 7 more CHD events, 8 more strokes, 8 more PEs, and 8 more invasive breast cancers, while absolute risk reductions per l0,000 women-years were 6 fewer colorectal cancers and 5 fewer hip fractures. The absolute excess risk of events included in the “global index” was 19 per 10,000 women-years. There was no difference between the groups in terms of all-cause mortality. (See BOXED WARNINGS , WARNINGS, and PRECAUTIONS.)

Women's Health Initiative Memory Study

The Women’s Health Initiative Memory Study (WHIMS), a substudy of WHI, enrolled 4,532 predominantly postmenopausal women 65 years of age and older (47% were age 65 to 69 years, 35% were 70 to 74 years, and 18% were 75 years of age and older) to evaluate the effects of CE/MPA (0.625 mg conjugated estrogens plus 2.5 mg medroxyprogesterone acetate) on the incidence of probable dementia (primary outcome) compared with placebo. After an average follow-up of 4 years, 40 women in the estrogen/progestin group (45 per 10,000 women-years) and 21 in the placebo group (22 per 10,000 women-years) were diagnosed with probable dementia. The relative risk of probable dementia in the hormone therapy group was 2.05 (95% CI, 1.21 to 3.48) compared to placebo. Differences between groups became apparent in the first year of treatment. It is unknown whether these findings apply to younger postmenopausal women. (See BOXED WARNINGS and WARNINGS, Dementia and PRECAUTIONS, Geriatric Use.)

INDICATIONS AND USAGE

Estradiol Transdermal System Continuous Delivery (Once-Weekly), USP is indicated in the:

1. Treatment of moderate to severe vasomotor symptoms associated with the menopause.
2. Treatment of moderate to severe symptoms of vulvar and vaginal atrophy associated with the menopause. When prescribing solely for the treatment of symptoms of vulvar and vaginal atrophy, topical vaginal products should be considered.
3. Treatment of hypoestrogenism due to hypogonadism, castration or primary ovarian failure.
4. Prevention of postmenopausal osteoporosis. When prescribing solely for the prevention of postmenopausal osteoporosis, therapy should only be considered for women at significant risk of osteoporosis and non-estrogen medications should be carefully considered.
  The mainstays for decreasing the risk of postmenopausal osteoporosis are weight bearing exercise, adequate calcium and vitamin D intake, and when indicated, pharmacologic therapy. Postmenopausal women require an average of 1500 mg/day of elemental calcium. Therefore, when not contraindicated, calcium supplementation may be helpful for women with suboptimal dietary intake. Vitamin D supplementation of 400 IU/day to 800 IU/day may also be required to ensure adequate daily intake in postmenopausal women.

CONTRAINDICATIONS

Estradiol Transdermal System Continuous Delivery (Once-Weekly) should not be used in women with any of the following conditions:

1. Undiagnosed abnormal genital bleeding.
2. Known, suspected, or history of cancer of the breast.
3. Known or suspected estrogen-dependent neoplasia.
4. Active deep vein thrombosis, pulmonary embolism or a history of these conditions.
5. Active or recent (e.g., within the past year) arterial thromboembolic disease (e.g., stroke, myocardial infarction).
6. Liver dysfunction or disease.
7. Estradiol Transdermal System Continuous Delivery (Once-Weekly) should not be used in patients with known hypersensitivity to its ingredients.
8. Known or suspected pregnancy. There is no indication for Estradiol Transdermal System Continuous Delivery (Once-Weekly) in pregnancy. There appears to be little or no increased risk of birth defects in children born to women who have used estrogens and progestins from oral contraceptives inadvertently during early pregnancy (see PRECAUTIONS).

WARNINGS

See BOXED WARNINGS.

Cardiovascular disorders

Estrogen and estrogen/progestin therapy has been associated with an increased risk of cardiovascular events such as myocardial infarction and stroke, as well as venous thrombosis and pulmonary embolism (venous thromboembolism or VTE). Should any of these occur or be suspected, estrogens should be discontinued immediately.

Risk factors for arterial vascular disease (e.g., hypertension, diabetes mellitus, tobacco use, hypercholesterolemia, and obesity) and/or venous thromboembolism (e.g., personal history or family history of VTE, obesity, and systemic lupus erythematosus) should be managed appropriately.

Coronary heart disease and stroke

In the Women’s Health Initiative (WHI) study, an increased risk of stroke was observed in women receiving oral CE compared to placebo.

In the CE/MPA substudy of WHI an increased risk of coronary heart disease (CHD) events (defined as nonfatal myocardial infarction and CHD death) was observed in women receiving CE/MPA compared to women receiving placebo (37 vs. 30 per 10,000 women-years). The increase in risk was observed in year one and persisted. (See CLINICAL PHARMACOLOGY, Clinical Studies.)

In the same substudy of WHI, an increased risk of stroke was observed in women receiving CE/MPA compared to women receiving placebo (29 vs. 21 per 10,000 women-years). The increase in risk was observed after the first year and persisted.

In postmenopausal women with documented heart disease (n = 2,763, average age 66.7 years) a controlled clinical trial of secondary prevention of cardiovascular disease (Heart and Estrogen/Progestin Replacement Study; HERS) treatment with CE/MPA (0.625 mg/2.5 mg per day) demonstrated no cardiovascular benefit. During an average follow-up of 4.1 years, treatment with CE/MPA did not reduce the overall rate of CHD events in postmenopausal women with established coronary heart disease. There were more CHD events in the CE/MPA-treated group than in the placebo group in year 1, but not during the subsequent years. Two thousand three hundred and twenty one women from the original HERS trial agreed to participate in an open-label extension of HERS, HERS II. Average follow-up in HERS II was an additional 2.7 years, for a total of 6.8 years overall. Rates of CHD events were comparable among women in the CE/MPA group and the placebo group in HERS, HERS II, and overall.

Venous thromboembolism (VTE)

In the Women’s Health Initiative (WHI) study, an increased risk of deep vein thrombosis was observed in women receiving CE compared to placebo.

In the CE/MPA substudy of WHI, a 2-fold greater rate of VTE, including deep venous thrombosis and pulmonary embolism, was observed in women receiving CE/MPA compared to women receiving placebo. The rate of VTE was 34 per 10,000 women-years in the CE/MPA group compared to 16 per 10,000 women-years in the placebo group. The increase in VTE risk was observed during the first year and persisted. (See CLINICAL PHARMACOLOGY, Clinical Studies.)

If feasible, estrogens should be discontinued at least 4 to 6 weeks before surgery of the type associated with an increased risk of thromboembolism, or during periods of prolonged immobilization.

Malignant neoplasms Endometrial cancer

The use of unopposed estrogens in women with intact uteri has been associated with an increased risk of endometrial cancer. The reported endometrial cancer risk among unopposed estrogen users is about 2-fold to 12-fold greater than in non-users, and appears dependent on duration of treatment and on estrogen dose. Most studies show no significant increased risk associated with use of estrogens for less than one year. The greatest risk appears associated with prolonged use, with increased risks of 15-fold to 24-fold for 5 to 10 years or more and this risk has been shown to persist for at least 8 to 15 years after estrogen therapy is discontinued.

Clinical surveillance of all women taking estrogen/progestin combinations is important. Adequate diagnostic measures, including endometrial sampling when indicated, should be undertaken to rule out malignancy in all cases of undiagnosed persistent or recurring abnormal vaginal bleeding. There is no evidence that the use of natural estrogens results in a different endometrial risk profile than synthetic estrogens of equivalent estrogen dose. Adding a progestin to estrogen therapy has been shown to reduce the risk of endometrial hyperplasia, which may be a precursor to endometrial cancer.

Breast cancer

The use of estrogens and progestins by postmenopausal women has been reported to increase the risk of breast cancer. The most important randomized clinical trial providing information about this issue is the Women’s Health Initiative (WHI) substudy of CE/MPA (see CLINICAL PHARMACOLOGY, Clinical Studies). The results from observational studies are generally consistent with those of the WHI clinical trial and report no significant variation in the risk of breast cancer among different estrogens or progestins, doses, or routes of administration.

The CE/MPA substudy of WHI reported an increased risk of breast cancer in women who took CE/MPA for a mean follow-up of 5.6 years. Observational studies have also reported an increased risk for estrogen/progestin combination therapy, and a smaller increased risk for estrogen alone therapy, after several years of use. In the WHI trial and from observational studies, the excess risk increased with duration of use. From observational studies, the risk appeared to return to baseline in about 5 years after stopping treatment. In addition, observational studies suggest that the risk of breast cancer was greater, and became apparent earlier, with estrogen/progestin combination therapy as compared to estrogen alone therapy.

In the CE/MPA substudy, 26% of the women reported prior use of estrogen alone and/or estrogen/progestin combination hormone therapy. After a mean follow-up of 5.6 years during the clinical trial, the overall relative risk of invasive breast cancer was 1.24 (95% confidence interval 1.01 - 1.54), and the overall absolute risk was 41 vs. 33 cases per 10,000 women-years, for CE/MPA compared with placebo. Among women who reported prior use of hormone therapy, the relative risk of invasive breast cancer was 1.86, and the absolute risk was 46 vs. 25 cases per 10,000 women-years, for CE/MPA compared with placebo. Among women who reported no prior use of hormone therapy, the relative risk of invasive breast cancer was 1.09, and the absolute risk was 40 vs. 36 cases per 10,000 women-years for CE/MPA compared with placebo. In the same substudy, invasive breast cancers were larger and diagnosed at a more advanced stage in the CE/MPA group compared with the placebo group. Metastatic disease was rare with no apparent difference between the two groups. Other prognostic factors such as histologic subtype, grade and hormone receptor status did not differ between the groups.

The use of estrogen plus progestin has been reported to result in an increase in abnormal mammograms requiring further evaluation. All women should receive yearly breast examinations by a healthcare provider and perform monthly breast self-examinations. In addition, mammography examinations should be scheduled based on patient age, risk factors, and prior mammogram results.

Dementia

In the Women’s Health Initiative Memory Study (WHIMS), 4,532 generally healthy postmenopausal women 65 years of age and older were studied, of whom 35% were 70 to 74 years of age and 18% were 75 or older. After an average follow-up of 4 years, 40 women being treated with CE/MPA (1.8%, n = 2,229) and 21 women in the placebo group (0.9%, n = 2,303) received diagnoses of probable dementia. The relative risk for CE/MPA versus placebo was 2.05 (95% confidence interval 1.21 - 3.48), and was similar for women with and without histories of menopausal hormone use before WHIMS. The absolute risk of probable dementia for CE/MPA versus placebo was 45 versus 22 cases per 10,000 women-years, and the absolute excess risk for CE/MPA was 23 cases per 10,000 women-years. It is unknown whether these findings apply to younger postmenopausal women. (See CLINICAL PHARMACOLOGY, Clinical Studies and PRECAUTIONS, Geriatric Use.)

Gallbladder disease

A 2-fold to 4-fold increase in the risk of gallbladder disease requiring surgery in postmenopausal women receiving estrogens has been reported.

Hypercalcemia

Estrogen administration may lead to severe hypercalcemia in patients with breast cancer and bone metastases. If hypercalcemia occurs, use of the drug should be stopped and appropriate measures taken to reduce the serum calcium level.

Visual abnormalities

Retinal vascular thrombosis has been reported in patients receiving estrogens. Discontinue medication pending examination if there is sudden partial or complete loss of vision, or a sudden onset of proptosis, diplopia, or migraine. If examination reveals papilledema or retinal vascular lesions, estrogens should be permanently discontinued.

PRECAUTIONS

General Addition of a progestin when a woman has not had a hysterectomy

Studies of the addition of a progestin for 10 or more days of a cycle of estrogen administration, or daily with estrogen in a continuous regimen, have reported a lowered incidence of endometrial hyperplasia than would be induced by estrogen treatment alone. Endometrial hyperplasia may be a precursor to endometrial cancer.

There are, however, possible risks that may be associated with the use of progestins with estrogens compared to estrogen-alone treatment. These include a possible increased risk of breast cancer.

Elevated blood pressure

In a small number of case reports, substantial increases in blood pressure have been attributed to idiosyncratic reactions to estrogens. In a large, randomized, placebo-controlled clinical trial, a generalized effect of estrogens on blood pressure was not seen. Blood pressure should be monitored at regular intervals with estrogen use.

Hypertriglyceridemia

In patients with preexisting hypertriglyceridemia, estrogen therapy may be associated with elevations of plasma triglycerides leading to pancreatitis and other complications.

Impaired liver function and past history of cholestatic jaundice

Estrogens may be poorly metabolized in patients with impaired liver function. For patients with a history of cholestatic jaundice associated with past estrogen use or with pregnancy, caution should be exercised and in the case of recurrence, medication should be discontinued.

Hypothyroidism

Estrogen administration leads to increased thyroid-binding globulin (TBG) levels. Patients with normal thyroid function can compensate for the increased TBG by making more thyroid hormone, thus maintaining free T4 and T3 serum concentrations in the normal range. Patients dependent on thyroid hormone replacement therapy who are also receiving estrogens may require increased doses of their thyroid replacement therapy. These patients should have their thyroid function monitored in order to maintain their free thyroid hormone levels in an acceptable range.

Fluid retention

Because estrogens may cause some degree of fluid retention, patients with conditions that might be influenced by this factor, such as a cardiac or renal dysfunction, warrant careful observation when estrogens are prescribed.

Hypocalcemia

Estrogens should be used with caution in individuals with severe hypocalcemia.

Ovarian cancer

The CE/MPA substudy of WHI reported that estrogen plus progestin increased the risk of ovarian cancer. After an average follow-up of 5.6 years, the relative risk for ovarian cancer for CE/MPA versus placebo was 1.58 (95% confidence interval 0.77-3.24) but was not statistically significant. The absolute risk for CE/MPA versus placebo was 4.2 versus 2.7 cases per 10,000 women-years. In some epidemiological studies, the use of estrogen alone, in particular for ten or more years, has been associated with an increased risk of ovarian cancer. Other epidemiologic studies have not found these associations.

Exacerbation of endometriosis

Endometriosis may be exacerbated with administration of estrogens. A few cases of malignant transformation of residual endometrial implants have been reported in women treated post-hysterectomy with estrogen alone therapy. For patients known to have residual endometriosis post-hysterectomy, the addition of progestin should be considered.

Exacerbation of other conditions

Estrogens may cause an exacerbation of asthma, diabetes mellitus, epilepsy, migraine or porphyria, systemic lupus erythematosus, and hepatic hemangiomas and should be used with caution in women with these conditions.

Patient Information

Physicians are advised to discuss the PATIENT INFORMATION leaflet with patients for whom they prescribe Estradiol Transdermal System Continuous Delivery (Once-Weekly).

Laboratory Tests

Estrogen administration should be initiated at the lowest dose approved for the indication and then guided by clinical response rather than by serum hormone levels (e.g., estradiol, FSH).

Drug/Laboratory Test Interactions

1. Accelerated prothrombin time, partial thromboplastin time, and platelet aggregation time; increased platelet count; increased factors II, VII antigen, VIII antigen, VIII coagulant activity, IX, X, XII, VII-X complex, II-VII-X complex, and beta-thromboglobulin; decreased levels of antifactor Xa and antithrombin III, decreased antithrombin III activity; increased levels of fibrinogen and fibrinogen activity; increased plasminogen antigen and activity.
2. Increased thyroid-binding globulin (TBG) levels leading to increased circulating total thyroid hormone levels as measured by protein bound iodine (PBI), T4 levels (by column or by radioimmunoassay) or T3 levels by radioimmunoassay. T3 resin uptake is decreased, reflecting the elevated TBG. Free T4 and free T3 concentrations are unaltered. Patients on thyroid replacement therapy may require higher doses of thyroid hormone.
3. Other binding proteins may be elevated in serum (i.e., corticosteroid binding globulin (CBG), sex hormone-binding globulin (SHBG)) leading to increased total circulating corticosteroids and sex steroids, respectively. Free hormone concentrations may be decreased. Other plasma proteins may be increased (angiotensinogen/renin substrate, alpha-1-antitrypsin, ceruloplasmin).
4. Increased plasma HDL and HDL2 cholesterol subfraction concentrations, reduced LDL cholesterol concentration, and in oral formulations increased triglyceride levels.
5. Impaired glucose tolerance.
6. Reduced response to metyrapone test.

Carcinogenesis, Mutagenesis, and Impairment of Fertility

Long-term continuous administration of estrogen, with and without progestin, in women with and without a uterus, has shown an increased risk of endometrial cancer, breast cancer, and ovarian cancer. (See BOXED WARNINGS, WARNINGS and PRECAUTIONS.)

Long-term continuous administration of natural and synthetic estrogens in certain animal species increases the frequency of carcinomas of the breast, uterus, cervix, vagina, testis, and liver.

Pregnancy

Estradiol Transdermal System Continuous Delivery (Once-Weekly) should not be used during pregnancy. (See CONTRAINDICATIONS.)

Nursing Mothers

Estrogen administration to nursing mothers has been shown to decrease the quantity and quality of the milk. Detectable amounts of estrogens have been identified in the milk of mothers receiving this drug. Caution should be exercised when Estradiol Transdermal System Continuous Delivery (Once-Weekly) is administered to a nursing woman.

Pediatric Use

Estrogen replacement therapy has been used for the induction of puberty in adolescents with some forms of pubertal delay. Safety and effectiveness in pediatric patients have not otherwise been established. Large and repeated doses of estrogen over an extended time period have been shown to accelerate epiphyseal closure, which could result in short adult stature if treatment is initiated before the completion of physiologic puberty in normally developing children. If estrogen is administered to patients whose bone growth is not complete, periodic monitoring of bone maturation and effects on epiphyseal centers is recommended during estrogen administration. Estrogen treatment of prepubertal girls also induces premature breast development and vaginal cornification, and may induce vaginal bleeding. In boys, estrogen treatment may modify the normal pubertal process and induce gynecomastia. (See INDICATIONS AND USAGE and DOSAGE AND ADMINISTRATION.)

Geriatric Use

There have not been sufficient numbers of geriatric patients involved in clinical studies utilizing Estradiol Transdermal System Continuous Delivery (Once-Weekly) to determine whether those over 65 years of age differ from younger subjects in their response to Estradiol Transdermal System Continuous Delivery (Once-Weekly).

In the Women’s Health Initiative Memory Study, including 4,532 women 65 years of age and older, followed for an average of 4 years, 82% (n = 3,729) were 65 to 74 while 18% (n = 803) were 75 and over. Most women (80%) had no prior hormone therapy use. Women treated with conjugated estrogens plus medroxyprogesterone acetate were reported to have a 2-fold increase in the risk of developing probable dementia. Alzheimer’s disease was the most common classification of probable dementia in both the conjugated estrogens plus medroxyprogesterone acetate group and the placebo group. Ninety percent of the cases of probable dementia occurred in the 54% of women that were older than 70. (See BOXED WARNING and WARNINGS, Dementia.)

ADVERSE REACTIONS

See BOXED WARNINGS, WARNINGS and PRECAUTIONS.

Because clinical trials are conducted under widely varying conditions, adverse reaction rates observed in the clinical trials of a drug cannot be directly compared to rates in the clinical trials of another drug and may not reflect the rates observed in practice. The adverse reaction information from clinical trials does, however, provide a basis for identifying the adverse events that appear to be related to drug use and for approximating rates.

Summary of Most Frequently Reported Adverse Experiences/Medical Events (Greater Than or Equal To 5%) by Treatment Groups
 | Estradiol | Transdermal | System
 | Continuous | Delivery | (Once-Weekly)
AE per Body System | 0.025 mg/day (N=219) | 0.05 mg/day (N=201) | 0.1 mg/day (N=194) | Placebo (N=72)
Body as a Whole | 21% | 39% | 37% | 29%
Headache | 5% | 18% | 13% | 10%
Pain | 1% | 8% | 11% | 7%
Back Pain | 4% | 8% | 9% | 6%
Edema | 0.5% | 13.% | 10% | 6%
Gastrointestinal | 9% | 21% | 29% | 18%
Abdominal Pain | 0.0% | 11% | 16% | 8%
Nausea | 1% | 5% | 6% | 3%
Flatulence | 1% | 3% | 7% | 1%
Musculoskeletal | 7% | 9% | 11% | 4%
Arthralgia | 1% | 5% | 5% | 3%
Psychiatric | 13% | 10% | 11% | 1%
Depression | 1% | 5% | 8% | 0%
Reproductive | 12% | 18% | 41% | 11%
Breast Pain | 5% | 8% | 29% | 4%
Leukorrhea | 1% | 6% | 7% | 1%
Respiratory | 15% | 26% | 29% | 14%
URTI | 6% | 17% | 17% | 8%
Pharyngitis | 0.5% | 3% | 7% | 3%
Sinusitis | 4% | $5 | 5% | 3%
Rhinitis | 2% | 4% | 6% | 1%
Skin and Appendages | 19% | 12% | 12% | 15%
Pruritus | 0.5% | 6% | 3% | 6%

Post-marketing Experience

The following adverse reactions have been identified during post approval use of Estradiol Transdermal System Continuous Delivery (Once-Weekly): a few cases in which there were a combination of the symptoms of generalized hives or rash with swelling of the throat or eyelid edema. Because these reactions are reported voluntarily from a population of uncertain size, it is not always possible to reliably estimate their frequency or establish a causal relationship to drug exposure.

The following additional adverse reactions have been reported with estrogen and/or progestin therapy.

Genitourinary system

Changes in vaginal bleeding pattern and abnormal withdrawal bleeding or flow; breakthrough bleeding; spotting; dysmenorrhea; increase in size of uterine leiomyomata; vaginitis, including vaginal candidiasis; change in amount of cervical secretion; changes in cervical ectropion; ovarian cancer; endometrial hyperplasia; endometrial cancer.

Breasts

Tenderness, enlargement, pain, nipple discharge, galactorrhea; fibrocystic breast changes; breast cancer.

Cardiovascular

Deep and superficial venous thrombosis; pulmonary embolism; thrombophlebitis; myocardial infarction; stroke; increase in blood pressure.

Gastrointestinal

Nausea, vomiting; abdominal cramps, bloating; cholestatic jaundice; increased incidence of gallbladder disease; pancreatitis, enlargement of hepatic hemangiomas.

Skin

Chloasma or melasma, which may persist when drug is discontinued; erythema multiforme; erythema nodosum; hemorrhagic eruption; loss of scalp hair; hirsutism; pruritus, rash.

Eyes

Retinal vascular thrombosis, intolerance to contact lenses.

Central nervous system

Headache; migraine; dizziness; mental depression; chorea; nervousness; mood disturbances; irritability; exacerbation of epilepsy, dementia.

Miscellaneous

Increase or decrease in weight; reduced carbohydrate tolerance; aggravation of porphyria; edema; arthalgias; leg cramps; changes in libido; anaphylactoid/anaphylactic reactions; hypocalcemia; exacerbation of asthma; increased triglycerides.

OVERDOSAGE

Serious ill effects have not been reported following acute ingestion of large doses of estrogen-containing oral contraceptives by young children. Overdosage of estrogen may cause nausea and vomiting, and withdrawal bleeding may occur in females.

DOSAGE AND ADMINISTRATION

When estrogen is prescribed for a postmenopausal woman with a uterus, progestin should also be initiated to reduce the risk of endometrial cancer. A woman without a uterus does not need progestin. Use of estrogen, alone or in combination with a progestin, should be with the lowest effective dose and for the shortest duration consistent with treatment goals and risks for the individual woman. Patients should be reevaluated periodically as clinically appropriate (e.g., 3 month to 6 month intervals) to determine if treatment is still necessary. (See BOXED WARNINGS and WARNINGS.) For women who have a uterus, adequate diagnostic measures, such as endometrial sampling, when indicated, should be undertaken to rule out malignancy in cases of undiagnosed persistent or recurring abnormal vaginal bleeding.

Patients should be started at the lowest dose. Six (7.75 cm^2, 11.625 cm^2, 15.5 cm^2, 18.6 cm^2, 23.25 cm^2 and 31 cm^2) Estradiol Transdermal Systems Continuous Delivery (Once-Weekly) are available. For the treatment of vasomotor symptoms, treatment should be initiated with the 7.75 cm^2 (0.025 mg/day) Estradiol Transdermal System Continuous Delivery (Once-Weekly) applied to the skin once weekly. The dose should be adjusted as necessary to control symptoms. Clinical responses (relief of symptoms) at the lowest effective dose should be the guide for establishing administration of the Estradiol Transdermal System Continuous Delivery (Once-Weekly), especially in women with an intact uterus. Attempts to taper or discontinue the medication should be made at 3 month to 6 month intervals. In women who are not currently taking oral estrogens, treatment with Estradiol Transdermal System Continuous Delivery (Once-Weekly) can be initiated at once. In women who are currently taking oral estrogen, treatment with the Estradiol Transdermal System Continuous Delivery (Once-Weekly) can be initiated one week after withdrawal of oral therapy or sooner if symptoms reappear in less than one week. For the prevention of postmenopausal osteoporosis, the minimum dose that has been shown to be effective is the 7.75 cm^2 (0.025 mg/day) Estradiol Transdermal System Continuous Delivery (Once-Weekly). Response to therapy can be assessed by biochemical markers and measurement of bone mineral density.

Application of the System

The adhesive side of the Estradiol Transdermal System Continuous Delivery (Once-Weekly) should be placed on a clean, dry area of the lower abdomen or the upper quadrant of the buttock. The Estradiol Transdermal System Continuous Delivery (Once-Weekly) should not be applied to or near the breasts. The sites of application must be rotated, with an interval of at least one week allowed between applications to a particular site. The area selected should not be oily, damaged, or irritated. The waistline should be avoided, since tight clothing may rub and remove the system. Application to areas where sitting would dislodge the system should also be avoided. The system should be applied immediately after opening the pouch and removing the protective liner. The system should be pressed firmly in place with the fingers for about 10 seconds, making sure there is good contact, especially around the edges. If the system lifts, apply pressure to maintain adhesion. In the event that a system should fall off, a new system should be applied for the remainder of the 7 day dosing interval. Only one system should be worn at any one time during the 7 day dosing interval. Swimming, bathing, or using a sauna while using the Estradiol Transdermal System Continuous Delivery (Once-Weekly) has not been studied, and these activities may decrease the adhesion of the system and the delivery of estradiol.

Removal of the System

Removal of the system should be done carefully and slowly to avoid irritation of the skin. Should any adhesive remain on the skin after removal of the system, allow the area to dry for 15 minutes. Then gently rubbing the area with an oil-based cream or lotion should remove the adhesive residue.

Used patches still contain some active hormones. Each patch should be carefully folded in half so that it sticks to itself before throwing it away.

HOW SUPPLIED

Estradiol Transdermal System, 0.025 mg/day Continuous Delivery (Once-Weekly), USP – each 7.75 cm^2 system contains 0.97 mg of estradiol USP

NDC 54868-5009-0 Individual Carton of 4 systems

Estradiol Transdermal System, 0.05 mg/day Continuous Delivery (Once-Weekly), USP – each 15.5 cm^2 system contains 1.94 mg of estradiol USP

NDC 54868-4811-0 Individual Carton of 4 systems

Estradiol Transdermal System, 0.1 mg/day Continuous Delivery (Once-Weekly), USP – each 31 cm^2 system contains 3.88 mg of estradiol USP

NDC 54868-4813-0 Individual Carton of 4 systems

Store at 20° to 25°C (68° to 77°F). [See USP for Controlled Room Temperature.] Do not store unpouched. Apply immediately upon removal from the protective pouch.

MYLAN PHARMACEUTICALS INC.
Morgantown, WV 26505

REVISED AUGUST 2008
ETS:R16

PATIENT INFORMATION

Estradiol Transdermal System
Continuous Delivery (Once-Weekly), USP
PATIENT INFORMATION

Read this PATIENT INFORMATION before you start using Estradiol Transdermal System Continuous Delivery (Once-Weekly), USP and read what you get each time you refill Estradiol Transdermal System Continuous Delivery (Once-Weekly), USP. There may be new information. This information does not take the place of talking to your healthcare provider about your medical condition or your treatment.

What is the most important information I should know about Estradiol Transdermal System Continuous Delivery (Once-Weekly) (an estrogen hormone)?

- Estrogens increase the chances of getting cancer of the uterus.

Report any unusual vaginal bleeding right away while you are taking estrogens. Vaginal bleeding after menopause may be a warning sign of cancer of the uterus (womb). Your healthcare provider should check any unusual vaginal bleeding to find out the cause.

- Do not use estrogens with or without progestins to prevent heart disease, heart attacks, strokes, or dementia.

Using estrogens with or without progestins may increase your chances of getting heart attack, strokes, breast cancer, and blood clots. Using estrogens with progestins may increase your risk of dementia. You and your healthcare provider should talk regularly about whether you still need treatment with Estradiol Transdermal System Continuous Delivery (Once-Weekly).

What is Estradiol Transdermal System Continuous Delivery (Once-Weekly)?

Estradiol Transdermal System Continuous Delivery (Once-Weekly) is a medicine that contains estrogen hormones.

What is Estradiol Transdermal System Continuous Delivery (Once-Weekly) used for?

Estradiol Transdermal System Continuous Delivery (Once-Weekly) is used after menopause to:

- reduce moderate to severe hot flashes. Estrogens are hormones made by a woman’s ovaries. The ovaries normally stop making estrogens when a woman is between 45 to 55 years old. This drop in body estrogen levels causes the “change of life” or menopause (the end of monthly menstrual periods). Sometimes, both ovaries are removed during an operation before natural menopause takes place. The sudden drop in estrogen levels causes “surgical menopause.”
  When the estrogen levels begin dropping, some women develop very uncomfortable symptoms, such as feelings of warmth in the face, neck, and chest, or sudden strong feelings of heat and sweating (“hot flashes” or “hot flushes”). In some women, the symptoms are mild, and they will not need estrogens. In other women, symptoms can be more severe. You and your healthcare provider should talk regularly about whether you still need treatment with Estradiol Transdermal System Continuous Delivery (Once-Weekly).
- treat moderate to severe dryness, itching, and burning in or around the vagina. You and your healthcare provider should talk regularly about whether you still need treatment with Estradiol Transdermal System Continuous Delivery (Once-Weekly) to control these problems. If you use Estradiol Transdermal System Continuous Delivery (Once-Weekly) only to treat your dryness, itching, and burning in and around your vagina, talk with your healthcare provider about whether a topical vaginal product would be better for you.
- treat certain conditions in which a young woman’s ovaries do not produce enough estrogen naturally.
- help reduce your chances of getting osteoporosis (thin weak bones). Osteoporosis from menopause is a thinning of the bones that makes them weaker and easier to break. If you use Estradiol Transdermal System Continuous Delivery (Once-Weekly) only to prevent osteoporosis from menopause, talk with your healthcare provider about whether a different treatment or medicine without estrogens might be better for you. You and your healthcare provider should talk regularly about whether you should continue with Estradiol Transdermal System Continuous Delivery (Once-Weekly).
  Weight bearing exercise, like walking or running, and taking calcium and vitamin D supplements may also lower your chances of getting postmenopausal osteoporosis. It is important to talk about exercise and supplements with your healthcare provider before starting them.

Who should not use Estradiol Transdermal System Continuous Delivery (Once-Weekly)?

Do not start using Estradiol Transdermal System Continuous Delivery (Once-Weekly) if you:

- have unusual vaginal bleeding.
- currently have or have had certain cancers. Estrogens may increase the chances of getting certain types of cancers, including cancer of the breast or uterus. If you have or had cancer, talk with your healthcare provider about whether you should take Estradiol Transdermal System Continuous Delivery (Once-Weekly).
- had a stroke or heart attack in the past year.
- currently have or have had blood clots.
- currently have or have had liver problems.
- are allergic to Estradiol Transdermal System Continuous Delivery (Once-Weekly) or any of its ingredients. See section titled “What are the ingredients in Estradiol Transdermal System Continuous Delivery (Once-Weekly)” at the end of this leaflet for a list of ingredients in Estradiol Transdermal System Continuous Delivery (Once-Weekly).
- think you may be pregnant.

Tell your healthcare provider:

- if you are breast-feeding. The hormone in Estradiol Transdermal System Continuous Delivery (Once-Weekly) can pass into your milk.
- about all of your medical problems. Your healthcare provider may need to check you more carefully if you have certain conditions, such as asthma (wheezing), epilepsy (seizures), migraine, endometriosis, lupus, problems with your heart, liver, thyroid, kidneys, or have high calcium levels in your blood.
- about all the medicines you take. This includes prescription and nonprescription medicines, vitamins, and herbal supplements. Some medicines may affect how Estradiol Transdermal System Continuous Delivery (Once-Weekly) works. Estradiol Transdermal System Continuous Delivery (Once-Weekly) may also affect how your other medicines work.
- if you are going to have surgery or will be on bed rest. You may need to stop taking estrogens.

How should I use Estradiol Transdermal System Continuous Delivery (Once-Weekly)?

Estradiol Transdermal System Continuous Delivery (Once-Weekly) is a patch that you wear on your skin. The estrogen in the Estradiol Transdermal System Continuous Delivery (Once-Weekly) passes through your skin. You must change your Estradiol Transdermal System Continuous Delivery (Once-Weekly) patch every 7 days (once a week). See the end of this leaflet for complete instructions on how to use Estradiol Transdermal System Continuous Delivery (Once-Weekly).

1. Start at the lowest dose and talk to your healthcare provider about how well that dose is working for you.
2. Estrogens should be used at the lowest dose possible for your treatment only as long as needed. You and your healthcare provider should talk regularly (for example, every 3 months to 6 months) about the dose you are taking and whether you still need treatment with Estradiol Transdermal System Continuous Delivery (Once-Weekly).

What are the possible side effects of estrogens?

Less common but serious side effects include:

- Breast cancer
- Cancer of the uterus
- Stroke
- Heart attack
- Blood clots
- Dementia
- Gallbladder disease
- Ovarian cancer

These are some of the warning signs of serious side effects:

- Breast lumps
- Unusual vaginal bleeding
- Dizziness and faintness
- Changes in speech
- Severe headaches
- Chest pain
- Shortness of breath
- Pains in your legs
- Changes in vision
- Vomiting

Call your healthcare provider right away if you get any of these warning signs, or any other unusual symptom that concerns you.

Common side effects include:

- Headache
- Breast pain
- Irregular vaginal bleeding or spotting
- Stomach/abdominal cramps, bloating
- Nausea and vomiting
- Hair loss

Other side effects include:

- High blood pressure
- Liver problems
- High blood sugar
- Fluid retention
- Enlargement of benign tumors of the uterus (“fibroids”)
- Vaginal yeast infection

These are not all the possible side effects of Estradiol Transdermal System Continuous Delivery (Once-Weekly). For more information, ask your healthcare provider or pharmacist.

What can I do to lower my chances of a serious side effect with Estradiol Transdermal System Continuous Delivery (Once-Weekly)?

Talk with your healthcare provider regularly about whether you should continue using Estradiol Transdermal System Continuous Delivery (Once-Weekly).

- If you have a uterus, talk to your healthcare provider about whether the addition of a progestin is right for you.
- See your healthcare provider right away if you get vaginal bleeding while using Estradiol Transdermal System Continuous Delivery (Once-Weekly).
- Have a breast exam and mammogram (breast X-ray) every year unless your healthcare provider tells you something else. If members of your family have had breast cancer or if you have ever had breast lumps or an abnormal mammogram, you may need to have breast exams more often.
- If you have high blood pressure, high cholesterol (fat in the blood), diabetes, are overweight, or if you use tobacco, you may have higher chances for getting heart disease. Ask your healthcare provider for ways to lower your chances for getting heart disease.

General information about safe and effective use of Estradiol Transdermal System Continuous Delivery (Once-Weekly)

Medicines are sometimes prescribed for conditions that are not mentioned in patient information leaflets. Do not take Estradiol Transdermal System Continuous Delivery (Once-Weekly) for conditions for which it was not prescribed. Do not give Estradiol Transdermal System Continuous Delivery (Once-Weekly) to other people, even if they have the same symptoms you have. It may harm them.

Keep Estradiol Transdermal System Continuous Delivery (Once-Weekly) out of the reach of children.

This leaflet provides a summary of the most important information about Estradiol Transdermal System Continuous Delivery (Once-Weekly). If you would like more information, talk with your healthcare provider or pharmacist. You can ask for information about Estradiol Transdermal System Continuous Delivery (Once-Weekly) that is written for health professionals. You can get more information by calling the toll free number 1-877-446-3679 (1-877-4-INFO-RX).

What are the ingredients in Estradiol Transdermal System Continuous Delivery (Once-Weekly)?

The active ingredient of Estradiol Transdermal System Continuous Delivery (Once-Weekly) is estradiol. Estradiol Transdermal System Continuous Delivery (Once-Weekly) also contains propylene glycol, povidone, anhydrous colloidal silicon dioxide, pressure sensitive acrylic adhesive, copolymer foam, polyester film, and brown ink (yellow iron oxide pigment, red iron oxide pigment and carbon black pigment).

Instructions for Use

How and Where to Apply the Estradiol Transdermal System Continuous Delivery (Once-Weekly) Patch

Each Estradiol Transdermal System Continuous Delivery (Once-Weekly) patch is individually sealed in a protective pouch. To open the pouch, hold it with the Estradiol Transdermal System Continuous Delivery (Once-Weekly) name facing you. Tear from top to bottom using the right side tear notch. Tear from left to right using the top tear notch. Pull the pouch open. The Estradiol Transdermal System Continuous Delivery (Once-Weekly) patch is the peach colored foam round disk attached to the clear protective release liner.

Apply the sticky side of the Estradiol Transdermal System Continuous Delivery (Once-Weekly) patch to a clean, dry area of the lower stomach below your belly button or the top of the buttocks (see diagram below). Do not apply the Estradiol Transdermal System Continuous Delivery (Once-Weekly) patch to your breasts. The sites of application on the lower stomach and buttocks must be rotated, allowing at least one week between applications to the same site. The site selected should not be oily, damaged, or irritated. Avoid the waistline, since tight clothing may rub and remove the patch. Also, do not put the patch on areas where sitting would rub it off or loosen it. Apply the patch right after opening the pouch and removing the protective liner. Press the patch firmly in place with your fingers for about 10 seconds. Make sure that it sticks all over, especially around the edges.

The Estradiol Transdermal System Continuous Delivery (Once-Weekly) patch should be worn continuously for one week. You may wish to try different sites when putting on a new patch, to find ones that are most comfortable for you and where clothing will not rub on the patch or loosen it.

When to Apply the Estradiol Transdermal System Continuous Delivery (Once-Weekly)?

The Estradiol Transdermal System Continuous Delivery (Once-Weekly) patch should be changed once weekly. Remove the used patch. Carefully fold it in half so that it sticks to itself because used patches still contain active hormones and discard it. Any adhesive that might remain on your skin can be easily rubbed off. Then place the new Estradiol Transdermal System Continuous Delivery (Once-Weekly) patch on a different skin site. (The same skin site should not be used again for at least one week after removal of the patch.)

Contact with water when you are bathing, swimming, or showering may affect the patch. If the patch falls off, the same patch may be reapplied to another area of the lower abdomen. Make sure that there is good contact, especially around the edges. If the patch will not stick completely to your skin, put a new patch on a different area of the lower abdomen. Do not apply two patches at the same time.

Estrogens should be used only as long as needed. You and your healthcare provider should talk regularly (for example, every 3 months to 6 months) about whether you still need treatment with Estradiol Transdermal System Continuous Delivery (Once-Weekly).

Call your doctor for medical advice about side effects. You may report side effects to FDA at 1-800-FDA-1088.

MYLAN PHARMACEUTICALS INC.
Morgantown, WV 26505

REVISED AUGUST 2008
PL:ETS:R11

PRINCIPAL DISPLAY PANEL

NDC 54868-5009-0

Estradiol
Transdermal System,
0.025 mg/day

NDC 54868-4811-0

Estradiol
Transdermal System,
0.05 mg/day

NDC 54868-4813-0

Estradiol
Transdermal System,
0.1 mg/day